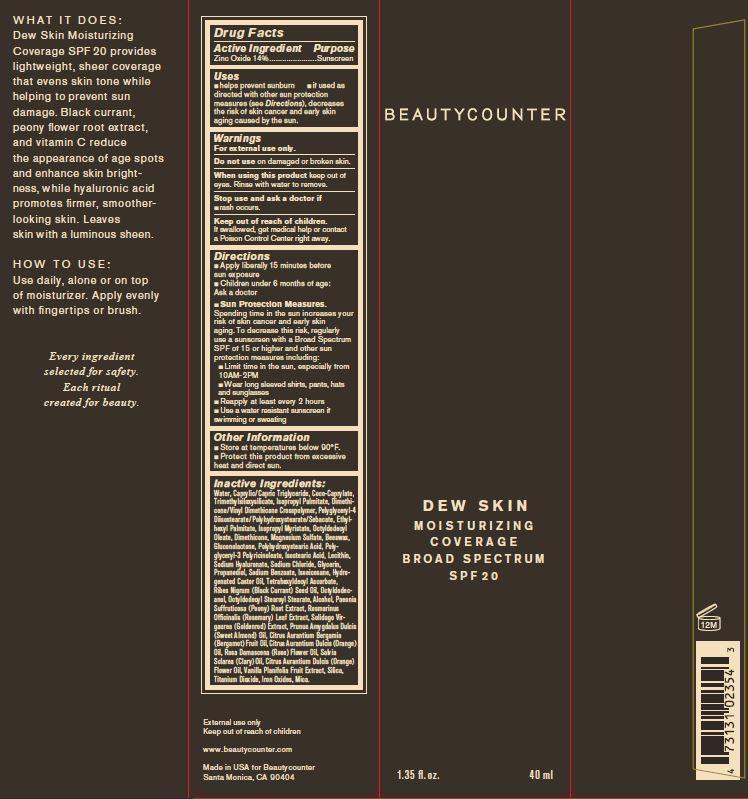 DRUG LABEL: Beauty Counter Dew Skin Moisturizer Tan
NDC: 69026-283 | Form: LOTION
Manufacturer: Beauty Counter, LLC
Category: otc | Type: HUMAN OTC DRUG LABEL
Date: 20200624

ACTIVE INGREDIENTS: ZINC OXIDE 14 g/100 mL
INACTIVE INGREDIENTS: ALCOHOL; YELLOW WAX; MEDIUM-CHAIN TRIGLYCERIDES; BERGAMOT OIL; CITRUS SINENSIS FLOWER OIL; ORANGE OIL; COCO-CAPRYLATE; DIMETHICONE; DIMETHICONE/VINYL DIMETHICONE CROSSPOLYMER (SOFT PARTICLE); ETHYLHEXYL PALMITATE; GLUCONOLACTONE; GLYCERIN; HYDROGENATED CASTOR OIL; ISOEICOSANE; ISOPROPYL MYRISTATE; ISOPROPYL PALMITATE; ISOSTEARIC ACID; EGG PHOSPHOLIPIDS; MAGNESIUM SULFATE, UNSPECIFIED; OCTYLDODECANOL; OCTYLDODECYL OLEATE; OCTYLDODECYL STEAROYL STEARATE; PAEONIA SUFFRUTICOSA ROOT; POLYGLYCERYL-3 RICINOLEATE; POLYGLYCERYL-4 ISOSTEARATE; POLYHYDROXYSTEARIC ACID (2300 MW); PROPANEDIOL; ALMOND OIL; RIBES NIGRUM SEED OIL; ROSA DAMASCENA FLOWER OIL; ROSEMARY; CLARY SAGE OIL; SILICON DIOXIDE; SODIUM BENZOATE; SODIUM CHLORIDE; HYALURONATE SODIUM; SOLIDAGO VIRGAUREA FLOWERING TOP; TETRAHEXYLDECYL ASCORBATE; TRIMETHYLSILOXYSILICATE (M/Q 0.8-1.0); VANILLA; TITANIUM DIOXIDE; FERRIC OXIDE YELLOW; FERRIC OXIDE RED; FERROSOFERRIC OXIDE; MICA; water

BeautyCounter Dew Skin Moisturizing Coverage SPF 20 Tan

Active Ingredients

Zinc Oxide - 14%

Purpose

Sunscreen

Uses

- Helps prevent sunburn
- if used as directed witho other sun production measures (see Directions), decreases the risk of skin cancer and early skin aging caused by the sun.

Warnings

For external use only.

Do not use

on damaged or broken skin.

When using this product

keep out of eyes. Rinse with water to remove.

Stop use and aks a doctor

if rash occurs

Keep out of reach of children.

If swallowed, get medical help or contact a Poison Control Center right away.

Directions

- Apply liberally 15 minutes before sun exposure
- Children under 6 months of age: Ask a doctor.
- Sun Protection Measures

Spending time in the sun increases you risk of skin cancer and early skin aging. To decrease this risk, regularly use a sunscreen with a Broad Spectrum SPF of 15 or higher and other sun protection measures including:

- Limit time in the sun, especially from 10AM-2PM
- Wear long sleeved shirts, pants, hats and sunglasses
- Reapply at leat every 2 hours
- Use a water resistant sunscreen if swimming or sweating.

Other Information

- Store at temperatures below 90°F.
- Protect this product from excessive heat and direct sun.

Inactive Ingredients:

Water, Caprylic/Capric Triglyceride, Coc-Caprylate, Trimethylsiloxysilicate, Isoprpyl Palmitate, Dimethicone/Vinyl Dimethicone Crosspolymer, Polyglyceryl-4 Diisostearate/Polyhydroxystearate/Sebacate, Ethylhexyl Palmitate, Isoproyl Myristate, Octyldodecyl Oleate, Dimethicone, Magnesium Sulfate, Beeswax, Glucolactone, Polyhydroxystearic Acid, Polyglyceryl-3 Polyricinoleate, Isostearic Acid, Lecithin, Sodium Hyaluronate, Sodium Chloride, Glycerin, Propanediol, Sodium Benzoate, Isoeicosane, Hydrogenated Castor Oil, Tetrahexyldecyl Ascorbate, Ribes Nigrum (Black Currant) Seed Oil, Octyldodecanol, Octyldodecyl Stearoyl Stearate, Alcohol, Paeonia Suffruticosa (Peony) Root Extract, Rosmarinus Officinalis (Rosemary) Leaf Extract, Solidago Virgqurea (Goldenrod) Extract, Prunus Amygdalus Dulcis (Sweet Almond) Oil, Citrus Aurantium Dulcis (Orange) Oil, Rosa Damascena (Rose) Flower Oil, Salvia Sclarea (Clary) Oil, Citrus Aurantium Dulcis (Orange) Flower Oil, Vanilla Planifolia Fruit Extract, Silica, Titanium Dioxide, Iron Oxides, Mica.